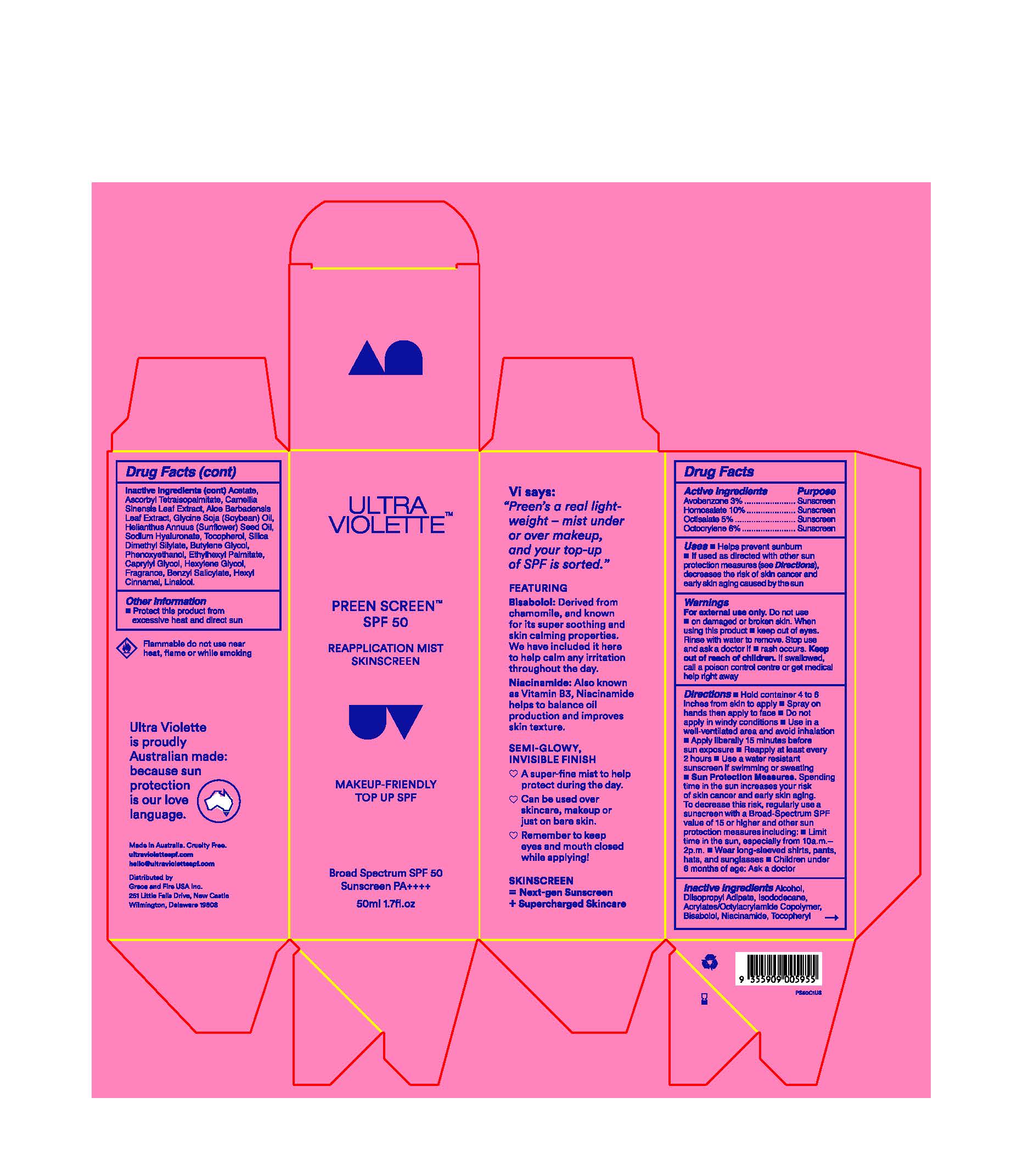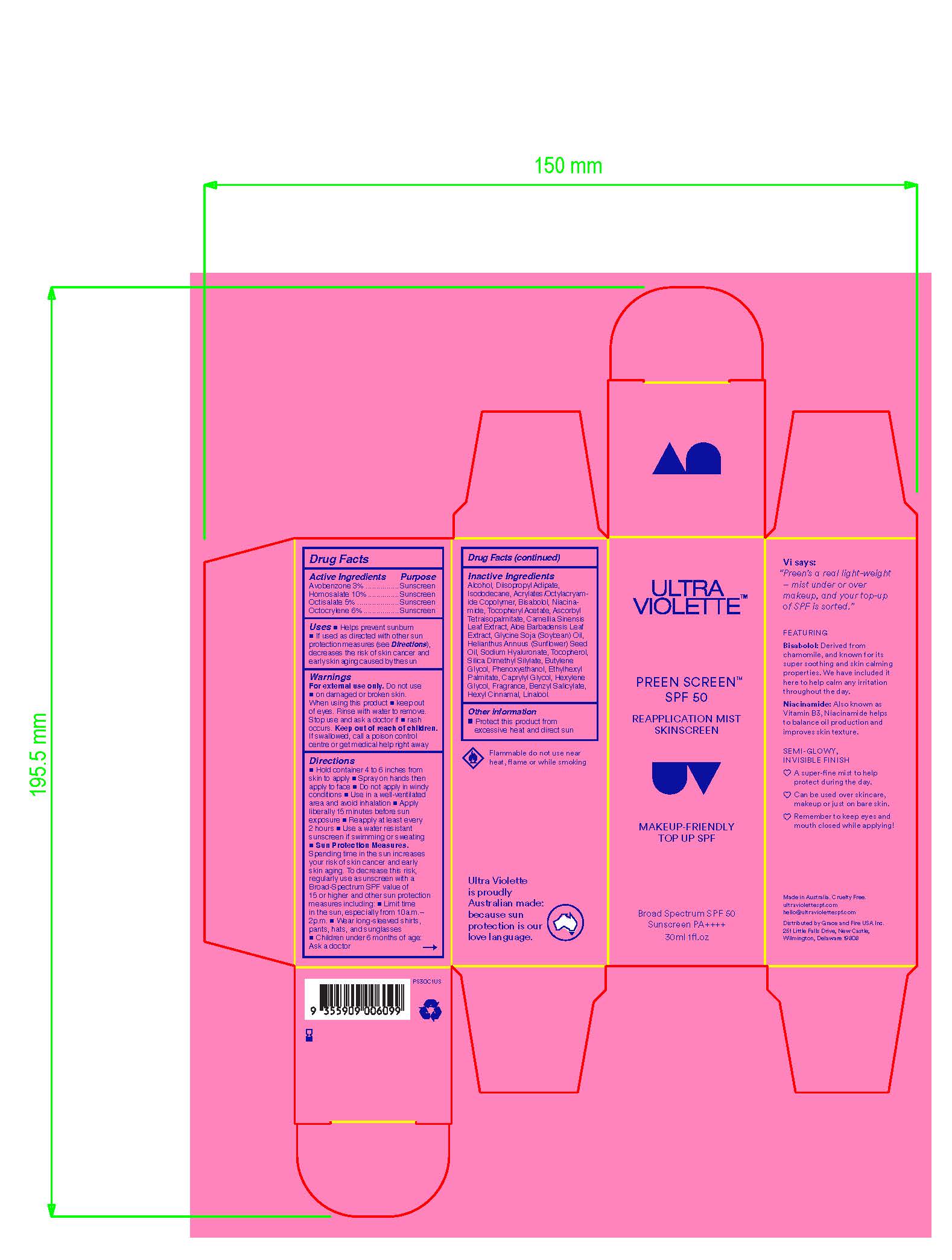 DRUG LABEL: Ultra Violette Preen Screen Broad Spectrum SPF 50
NDC: 84803-101 | Form: SPRAY
Manufacturer: Grace and Fire USA Inc.
Category: otc | Type: HUMAN OTC DRUG LABEL
Date: 20260105

ACTIVE INGREDIENTS: OCTISALATE 50 mg/1 mL; OCTOCRYLENE 60 mg/1 mL; HOMOSALATE 100 mg/1 mL; AVOBENZONE 30 mg/1 mL
INACTIVE INGREDIENTS: ALCOHOL; PHENOXYETHANOL; ISODODECANE; .ALPHA.-TOCOPHEROL ACETATE; SODIUM HYALURONATE; BENZYL SALICYLATE; LINALOOL, (-)-; CAMELLIA SINENSIS LEAF OIL; HELIANTHUS ANNUUS (SUNFLOWER) SEED; BISABOLOL; GLYCINE SOJA (SOYBEAN) OIL UNSAPONIFIABLES; ETHYLHEXYL PALMITATE; CAPRYLYL GLYCOL; SILICA DIMETHYL SILYLATE; ALOE BARBADENSIS LEAF; DIISOPROPYL ADIPATE; ASCORBYL TETRAISOPALMITATE; BUTYLENE GLYCOL; HEXYL CINNAMAL; HEXYLENE GLYCOL; NIACINAMIDE; ACRYLATES/OCTYLACRYLAMIDE COPOLYMER (40000 MW)

Principal Display Panel

Ultra Violette

Preen Screen Broad Spectrum SPF 50 Reapplication Mist Skinscreen

1.7 FL. OZ. (50 mL) 1 FL. OZ (30mL)